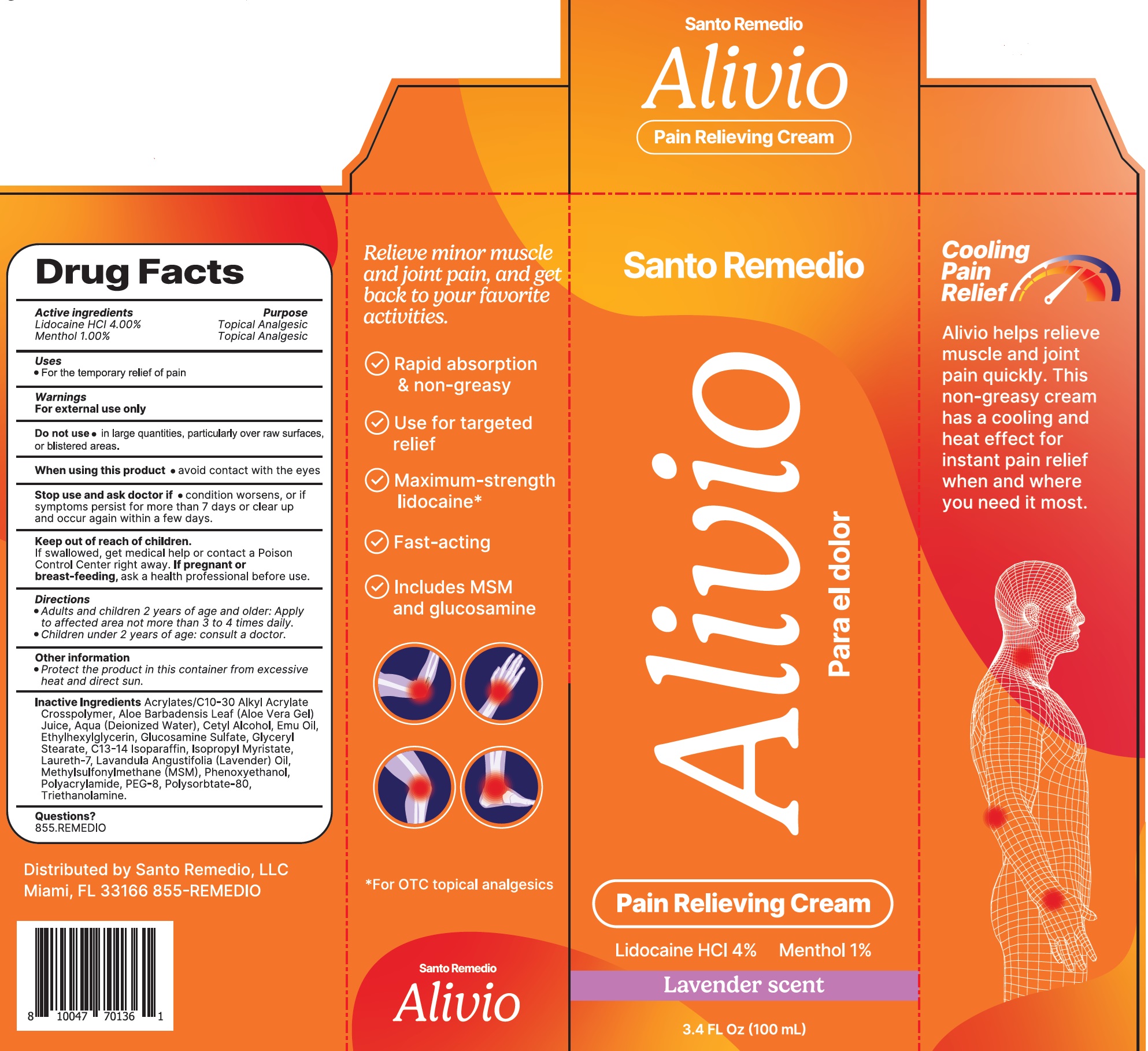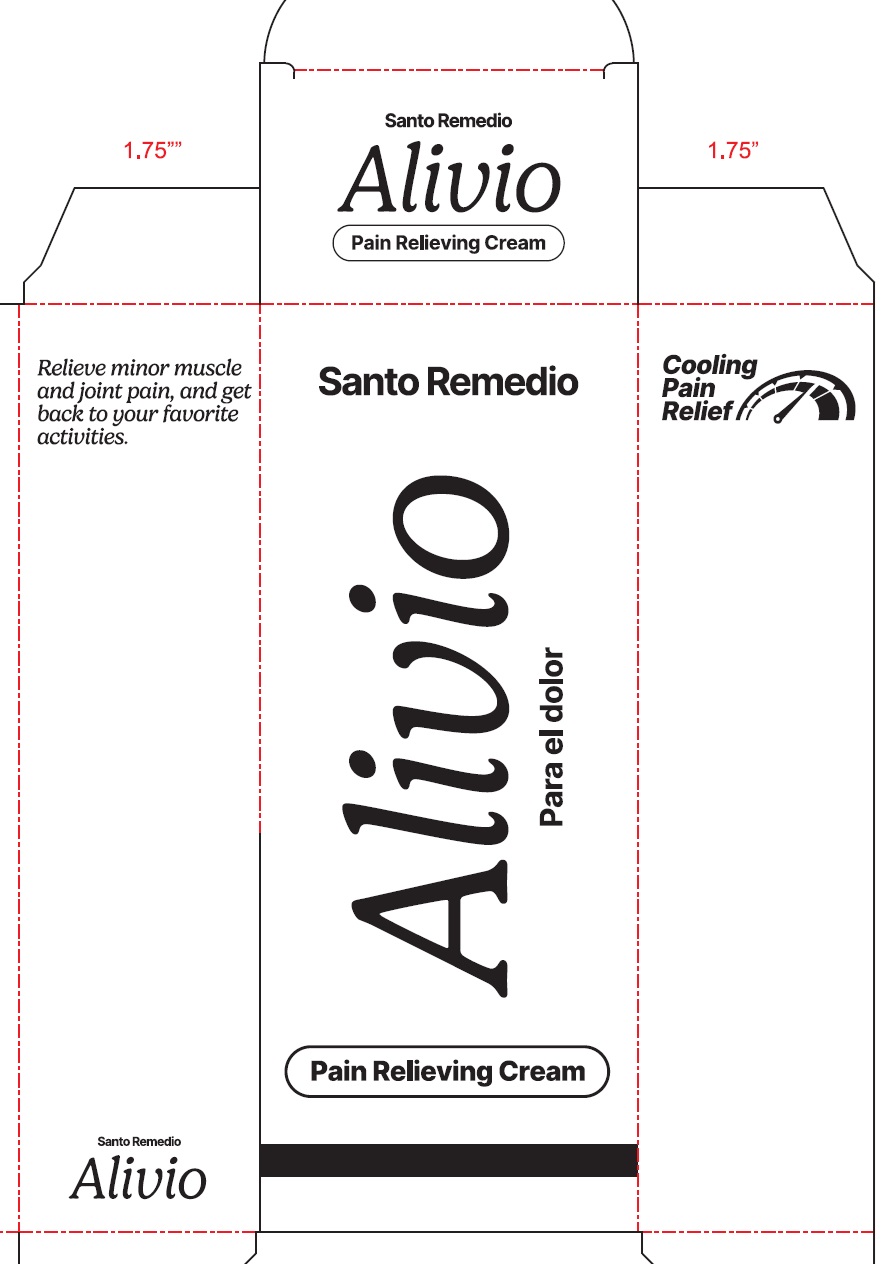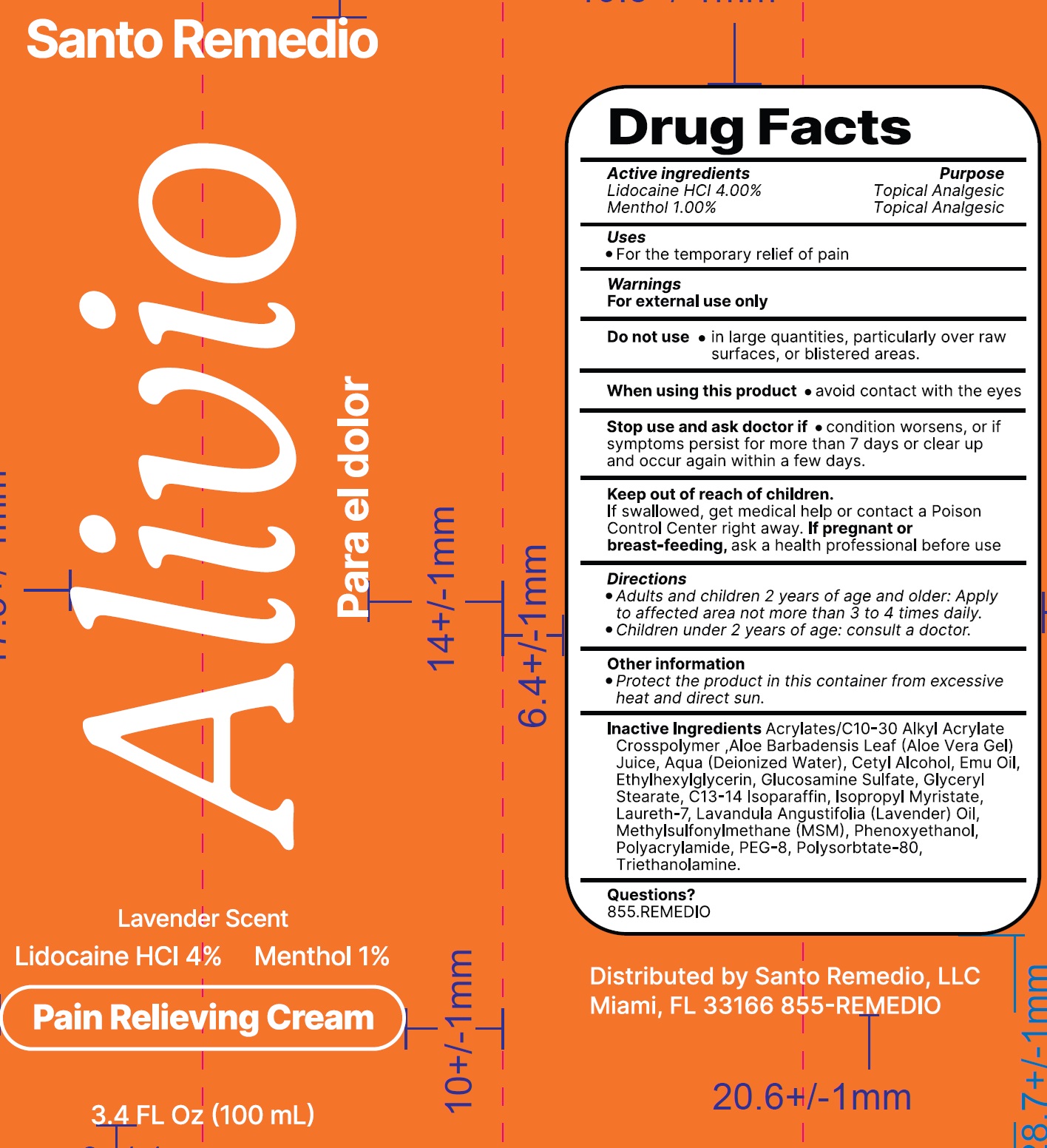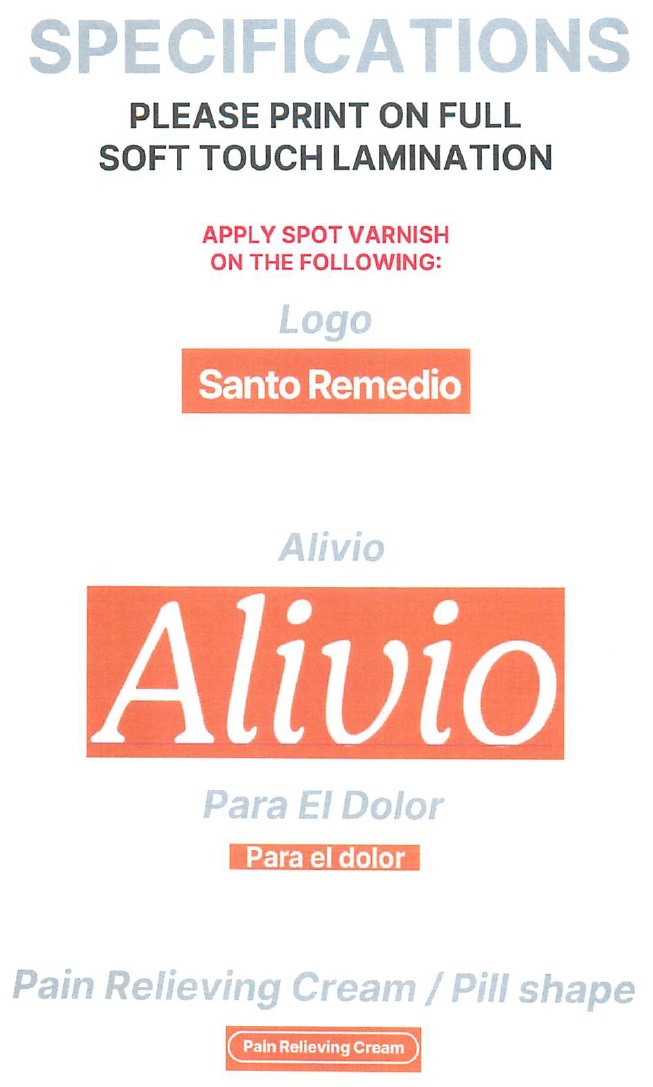 DRUG LABEL: SANTO REMEDIO Alivio Pain Relieving Lavender Scent
NDC: 81352-519 | Form: CREAM
Manufacturer: SANTO REMEDIO LLC
Category: otc | Type: HUMAN OTC DRUG LABEL
Date: 20240805

ACTIVE INGREDIENTS: LIDOCAINE HYDROCHLORIDE 40 mg/1 mL; MENTHOL 10 mg/1 mL
INACTIVE INGREDIENTS: ALOE VERA LEAF; WATER; CETYL ALCOHOL; EMU OIL; ETHYLHEXYLGLYCERIN; GLUCOSAMINE SULFATE; GLYCERYL MONOSTEARATE; C13-14 ISOPARAFFIN; ISOPROPYL MYRISTATE; LAURETH-7; LAVENDER OIL; DIMETHYL SULFONE; PHENOXYETHANOL; POLYETHYLENE GLYCOL 400; POLYSORBATE 80; TROLAMINE

SANTO REMEDIO Alivio Pain Relieving Cream Lavender Scent

Active ingredients

Lidocaine HCl 4.00%
Menthol 1.00%

Purpose

Topical Analgesic

Uses

- For the temporary relief of pain

Warnings

For external use only

Do not use

- in large quantities, particularly over raw surfaces, or blistered areas.

When using this product

- avoid contact with the eyes

Stop use and ask doctor if

- condition worsens, or if symptoms persist for more than 7 days or clear up and occur again within a few days.

Keep out of reach of children.

If swallowed, get medical help or contact a Poison Control Center right away.

If pregnant or breast-feeding,

ask a health professional before use.

Directions

- Adults and children 2 years of age and older: Apply to affected area not more than 3 to 4 times daily.
- Children under 2 years of age: consult a doctor.

Other information

- Protect the product in this container from excessive heat and direct sun.

Inactive Ingredients

Acrylates/C10-30 Alkyl Acrylate Crosspolymer, Aloe Barbadensis Leaf (Aloe Vera Gel) Juice, Aqua (Deionized Water), Cetyl Alcohol, Emu Oil, Ethylhexylglycerin, Glucosamine Sulfate, Glyceryl Stearate, C13-14 Isoparaffin, Isopropyl Myristate, Laureth-7, Lavandula Angustifolia (Lavender) Oil, Methylsulfonylmethane (MSM), Phenoxyethanol, Polyacrylamide, PEG-8, Polysorbtate-80, Triethanolamine.

Questions?

855.REMEDIO